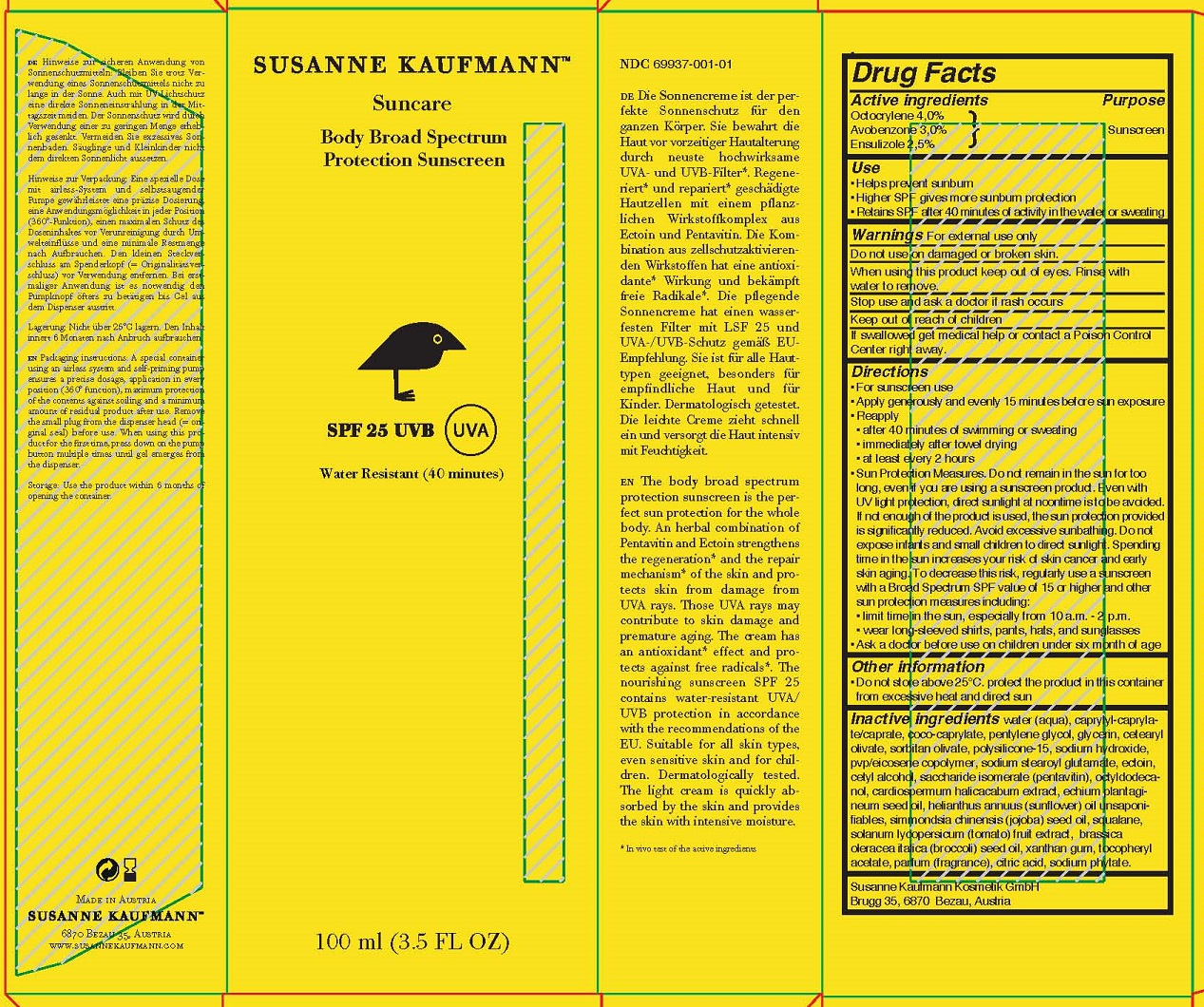 DRUG LABEL: SUSANNE KAUFMANN SUNCARE BODY BROAD SPECTRUM PROTECTION SUNSCREEN
NDC: 69937-001 | Form: LOTION
Manufacturer: Susanne Kaufmann Kosmetik GmbH
Category: otc | Type: HUMAN OTC DRUG LABEL
Date: 20170716

ACTIVE INGREDIENTS: OCTOCRYLENE 4 mg/100 mL; AVOBENZONE 3 mg/100 mL; ENSULIZOLE 2.5 mg/100 mL
INACTIVE INGREDIENTS: SODIUM HYDROXIDE; BROCCOLI SEED OIL; CITRIC ACID MONOHYDRATE; CETEARYL OLIVATE; SORBITAN OLIVATE; POLYSILICONE-15; EICOSYL POVIDONE; SODIUM STEAROYL GLUTAMATE; ECTOINE; CETYL ALCOHOL; SACCHARIDE ISOMERATE; OCTYLDODECANOL; CARDIOSPERMUM HALICACABUM WHOLE; ECHIUM PLANTAGINEUM SEED OIL; SUNFLOWER OIL; JOJOBA OIL; SQUALANE; TOMATO; XANTHAN GUM; .ALPHA.-TOCOPHEROL ACETATE; PHYTATE SODIUM; WATER; CAPRYLYL CAPRYLATE/CAPRATE; COCO-CAPRYLATE; PENTYLENE GLYCOL; GLYCERIN

ACTIVE INGREDIENT

Octocrylene 4.0%

Avobenzone 3.0%

Ensulizole 2.5%

PURPOSE

Sunscreen

INDICATIONS AND USAGE

Helps prevent sunburn

WARNINGS

For external use only

Do not use on damaged or broken skin.

When using this product keep out of eyes. Rinse with water to remove.

Stop use and ask a doctor if rash occurs

Keep out of reach of children

DOSAGE AND ADMINISTRATION

- Apply generously and evenly 15 minutes before sun exposure

- Reapply
- after 40 minutes of swimming or sweating
- immediately after towel drying
- at least every 2 hours

- Sun Protection Measures. Do not remain in the sun for too long, even if you are using a sunscreen product. Even with UV light protection, direct sunlight at noontime is to be avoided. If not enough of the product is used, the sun protection provided is significantly reduced. Avoid excessive sunbathing. Do not expose infants and small children to direct sunlight. Spending time in the sun increases your risk of skin cancer and early skin aging. To decrease this risk, regularly use a sunscreen with a Broad Spectrum SPF value of 15 or higher and other sun protection measures including:
- limit time in the sun, especially from 10 a.m. - 2 p.m.
- wear long-sleeved shirts, pants, hats, and sunglasses

Ask a doctor before use on children under six month of age

OTHER SAFETY INFORMATION

Do not store above 25°C. protect the product in this container from excessive heat and direct sun

INACTIVE INGREDIENT

water (aqua), caprylyl-caprylate/caprate, coco-caprylate, pentylene glycol, glycerin, cetearyl olivate, sorbitan olivate, polysilicone-15, sodium hydroxide, pvp/eicosene copolymer, sodium stearoyl glutamate, ectoin, cetyl alcohol, saccharide isomerate (pentavitin), octyldodecanol, cardiospermum halicacabum extract, echium plantagineum seed oil, helianthus annuus (sunflower) oil unsaponifiables, simmondsia chinensis (jojoba) seed oil, squalane, solanum lycopersicum (tomato) fruit extract, brassica oleracea italica (broccoli) seed oil, xanthan gum, tocopheryl acetate, parfum (fragrance), citric acid, sodium phytate.